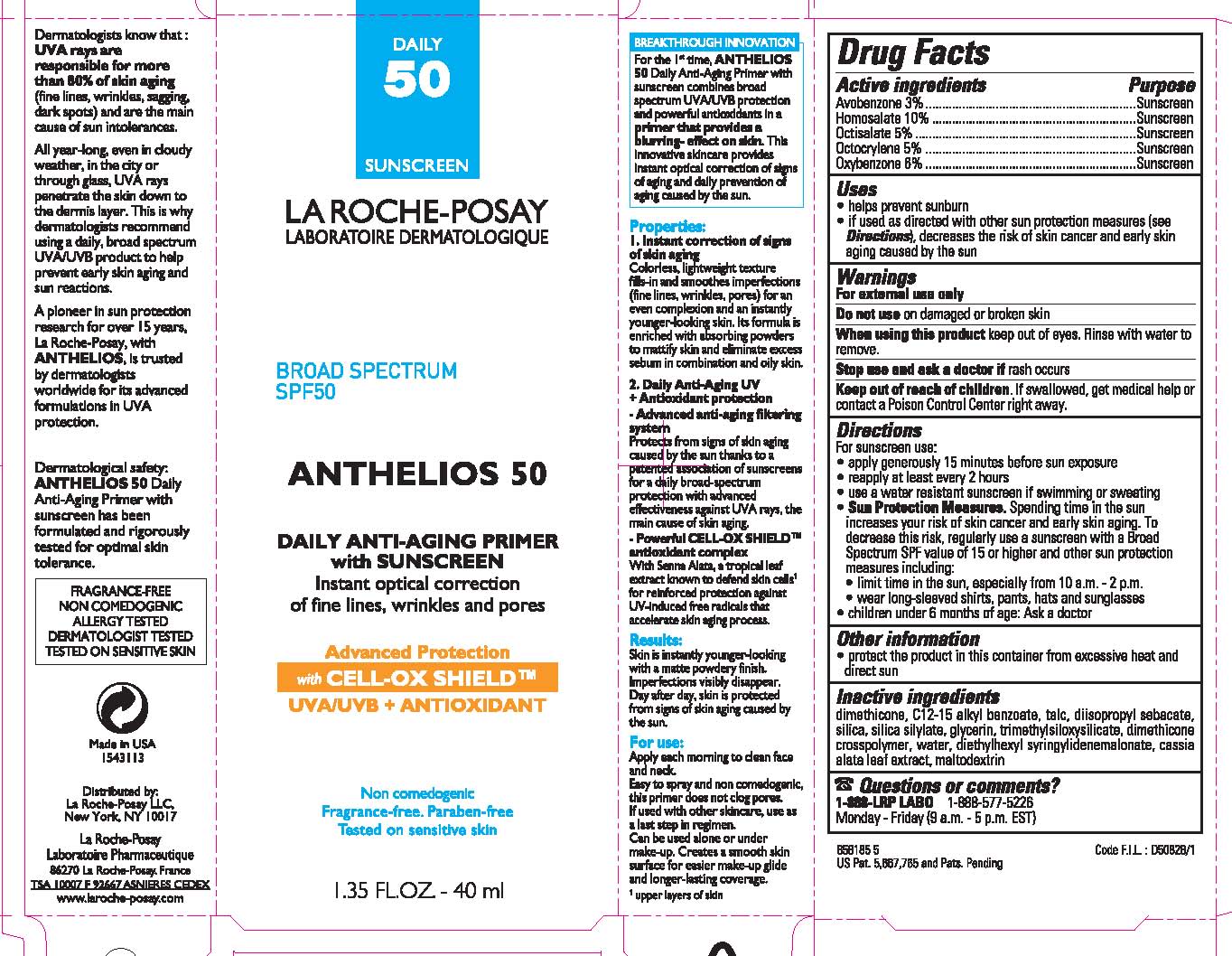 DRUG LABEL: La Roche Posay Laboratoire Dermatologique Anthelios 50 Daily Antiaging Primer with Sunscreen
NDC: 49967-095 | Form: LOTION
Manufacturer: L'Oreal USA Products Inc
Category: otc | Type: HUMAN OTC DRUG LABEL
Date: 20231231

ACTIVE INGREDIENTS: Avobenzone 30 mg/1 mL; Homosalate 100 mg/1 mL; Octisalate 50 mg/1 mL; Octocrylene 50 mg/1 mL; Oxybenzone 60 mg/1 mL
INACTIVE INGREDIENTS: DIMETHICONE; ALKYL (C12-15) BENZOATE; TALC; DIISOPROPYL SEBACATE; SILICON DIOXIDE; GLYCERIN; TRIMETHYLSILOXYSILICATE (M/Q 0.6-0.8); DIMETHICONE CROSSPOLYMER (450000 MPA.S AT 12% IN CYCLOPENTASILOXANE); WATER; DIETHYLHEXYL SYRINGYLIDENEMALONATE; SENNA ALATA LEAF; MALTODEXTRIN

Drug Facts

Active ingredients

Avobenzone 3%

Homosalate 10%

Octisalate 5%

Octocrylene 5%

Oxybenzone 6%

Uses

- helps prevent sunburn
- if used as directed (see Directions), decreases the risk of skin cancer and early skin aging caused by the sun

Warnings

For external use only

Do not use

on damaged or broken skin

When using this product

keep out of eyes. Rinse with water to remove.

Stop use and ask a doctor if

rash occurs

Keep out of reach of children.

If swallowed, get medical help or contact a Poison Control Center right away.

Directions

For sunscreen use:

- apply generously 15 minutes before sun exposure
- reapply at least every 2 hours
- use a water resistant sunscreen if swimming or sweating
- Sun Protection Measures. Spending time in the sun increases your risk of skin cancer and early skin aging. To decrease this risk regularly use a sunscreen with a Broad Spectrum SPF value of 15 of higher and other sun protection measures including:

- limit time in the sun, especially from 10 a.m. - 2 p.m.

- wear long-sleeved shirts, pants, hats and sunglasses

- children under 6 months of age: Ask a doctor

Purpose

Sunscreen

Other information

- protect the product in this container from excessive heat and direct sun

Inactive ingredients

dimethicone, C12-15 alkyl benzoate, talc, diisopropyl sebacate, silica, silica silylate, glycerin, trimethylsiloxysilicate, dimethicone crosspolymer, water, diethylhexyl syringylidenemalonate, cassia alata leaf extract, maltodextrin

Questions or comments?

1-888-LRP-LABO 1-888-577-5226

Monday - Friday (9 a.m. - 5 p.m. EST)